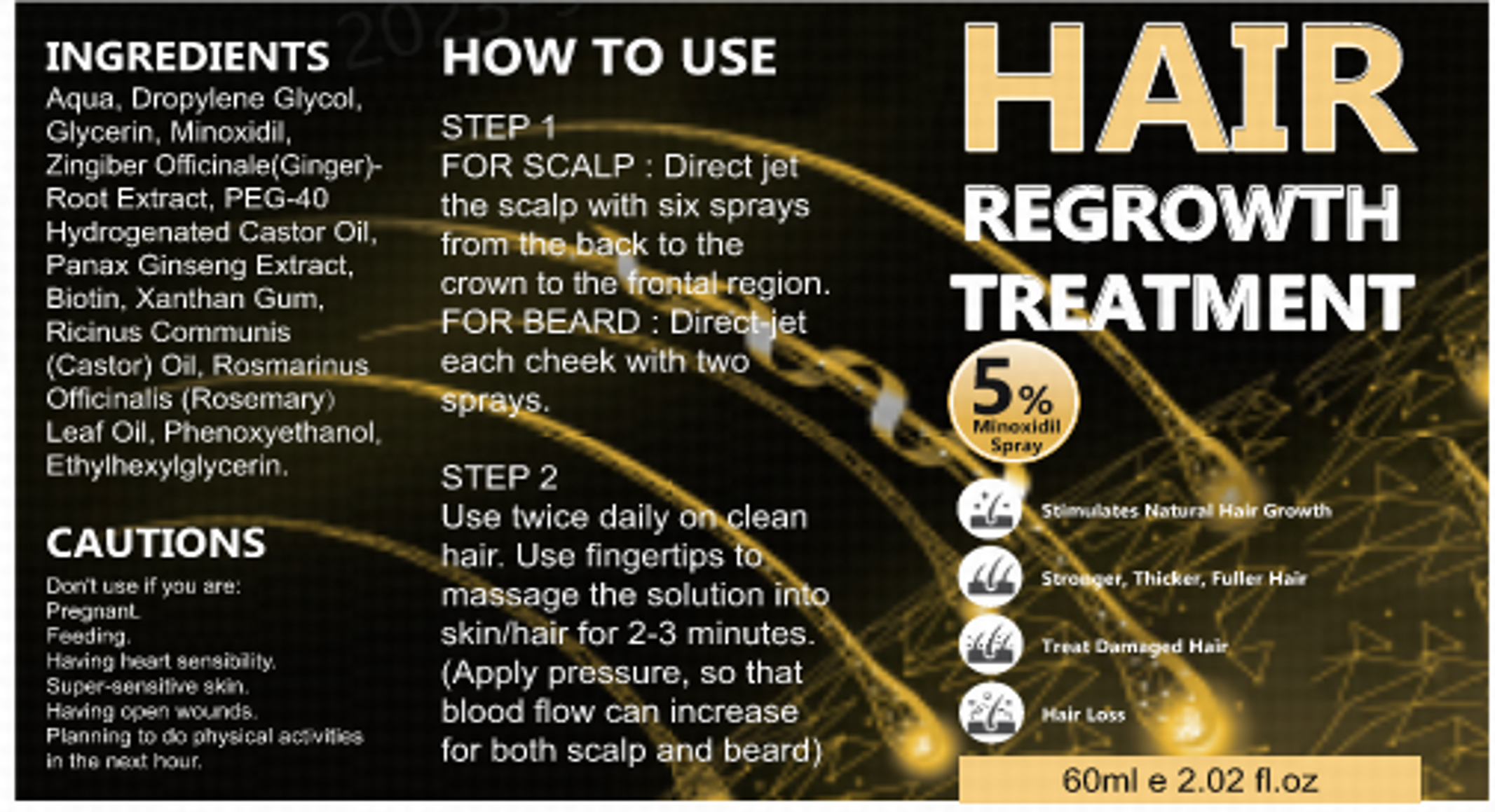 DRUG LABEL: Minoxidil Hair Growth Sprays
NDC: 83788-201 | Form: LIQUID
Manufacturer: Xiamen Panmai Technology Co., Ltd
Category: otc | Type: HUMAN OTC DRUG LABEL
Date: 20240704

ACTIVE INGREDIENTS: MINOXIDIL 5 g/100 mL
INACTIVE INGREDIENTS: GLYCERIN; WATER; PROPYLENE GLYCOL

Minoxidil Hair Growth Spray

Minoxidil Hair Growth Spray

ACTIVE INGREDIENT

Minoxidil 5%

PURPOSE

HAIR REGROW THTREATMENT

INDICATIONS AND USAGE

Stimubtes Natural Hair Growth
Strouger, Thicker, Fuller Hair
Treat Oameged Hair

WARNINGS

Don't use if you are:PregnanL
Feeding.
Haring heart gergiolity
Super-8engitie skin
Haing open wounds
Planning to do ahysical ac vitigs in the meat hour.

Don't use if you are:PregnanL
Feeding.
Haring heart gergiolity
Super-8engitie skin
Haing open wounds
Planning to do ahysical ac vitigs in the meat hour.

WHEN USING

STEP 1
FOR SCALP : Direct jet the scalp with six sprays from the back to the crown to the frontal region.FOR BEARD : Direct-jet each cheek with two sprays.
STEP 2
Use twice daily on clean hair. Use fingertips to massage the solution intoskin/hair for 2-3 minutes(Apply pressure, so thatblood flow can increase for both scalp and beard)

STOP USE

If there are adverse reactions such as itching and redness, please stop using immediately and seek medical help.

Keep out of reach of children.

DOSAGE AND ADMINISTRATION

Use twice daily on clean hair. Use fingertips to massage the solution intoskin/hair for 2-3 minutes(Apply pressure, so thatblood flow can increase for both scalp and beard)

STORAGE AND HANDLING

store at room temperature

INACTIVE INGREDIENT

Aqua
Propylene Glycol
Glycerin